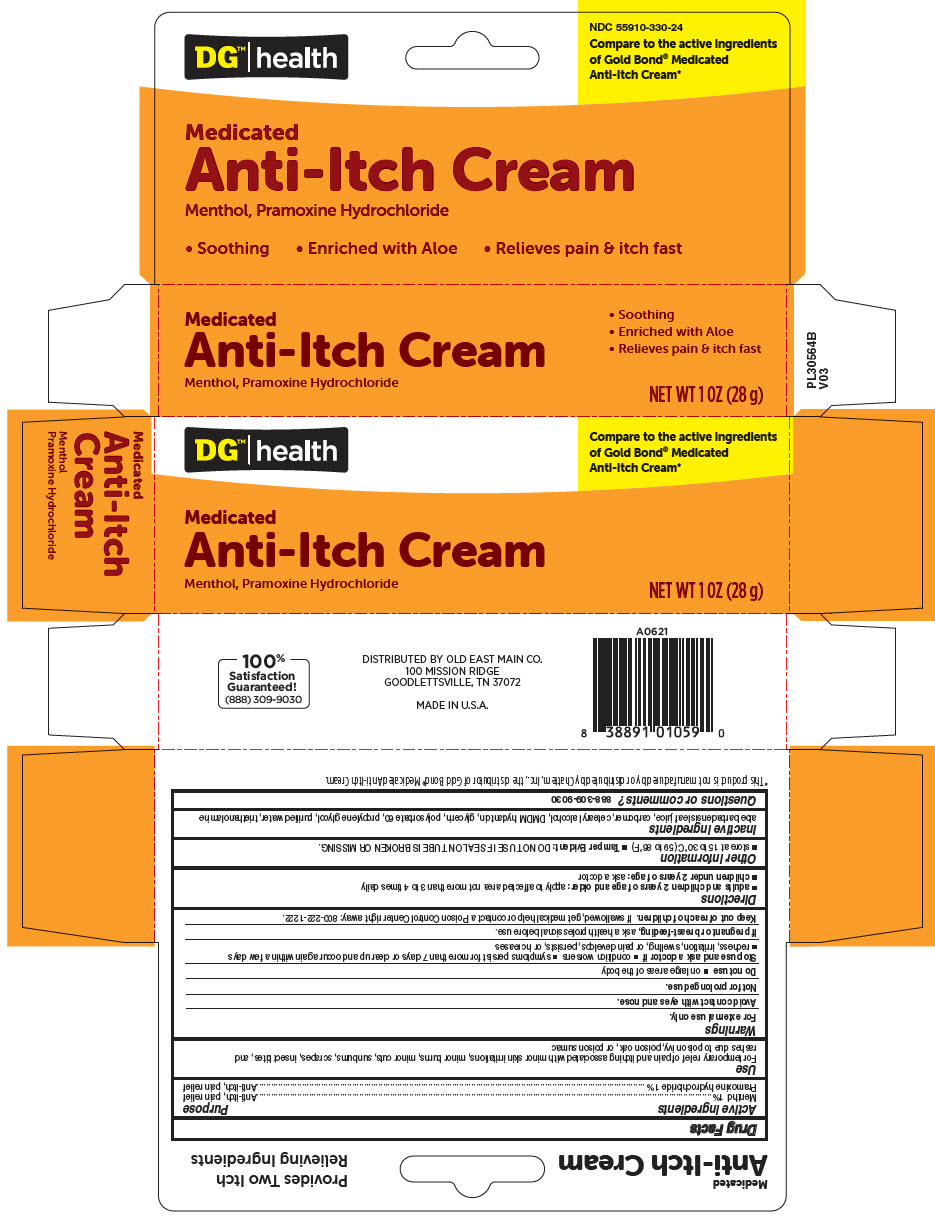 DRUG LABEL: DG Health Medicated Anti-Itch
NDC: 55910-330 | Form: CREAM
Manufacturer: DOLGENCORP, LLC
Category: otc | Type: HUMAN OTC DRUG LABEL
Date: 20200825

ACTIVE INGREDIENTS: Menthol, Unspecified Form 10 mg/1 g; Pramoxine Hydrochloride 10 mg/1 g
INACTIVE INGREDIENTS: Aloe Vera Leaf; CARBOMER HOMOPOLYMER TYPE C (ALLYL PENTAERYTHRITOL CROSSLINKED); DMDM HYDANTOIN; CETOSTEARYL ALCOHOL; POLYSORBATE 60; GLYCERIN; PROPYLENE GLYCOL; TROLAMINE; WATER

DG™ Health Medicated Anti-Itch Cream
Topical Analgesic

Drug Facts

ACTIVE INGREDIENT

Active ingredients | Purpose
Menthol 1% | Anti-itch, pain relief
Pramoxine hydrochloride 1% | Anti-itch, pain relief

Use

For temporary relief of pain and itching associated with minor skin irritations, minor burns, minor cuts, sunburns, scrapes, insect bites, and rashes due to poison ivy, poison oak, or poison sumac

Warnings

For external use only.

Avoid contact with eyes and nose.

Not for prolonged use.

Do not use

- on large areas of the body

Stop use and ask a doctor if

- condition worsens
- symptoms persist for more than 7 days or clear up and occur again within a few days
- redness, irritation, swelling, or pain develops, persists, or increases

PREGNANCY OR BREAST FEEDING

If pregnant or breast-feeding, ask a health professional before use.

Keep out of reach of children. If swallowed, get medical help or contact a Poison Control Center right away: 800-222-1222.

Directions

- adults and children 2 years of age and older: apply to affected area not more than 3 to 4 times daily
- children under 2 years of age: ask a doctor

Other information

- store at 15 to 30°C (59 to 86°F)
- Tamper Evident: DO NOT USE IF SEAL ON TUBE IS BROKEN OR MISSING.

Inactive ingredients

aloe barbadensis leaf juice, carbomer, cetearyl alcohol, DMDM hydantoin, glycerin, polysorbate 60, propylene glycol, purified water, triethanolamine

Questions or comments?

888-309-9030

DISTRIBUTED BY OLD EAST MAIN CO.
100 MISSION RIDGE
GOODLETTSVILLE, TN 37072

PRINCIPAL DISPLAY PANEL - 28 g Tube Carton

DG™| health

Compare to the active ingredients
of Gold Bond® Medicated
Anti-Itch Cream*

Medicated
Anti-Itch Cream
Menthol, Pramoxine Hydrochloride

NET WT 1 OZ (28 g)